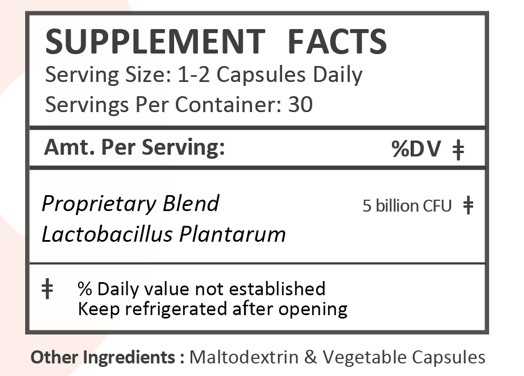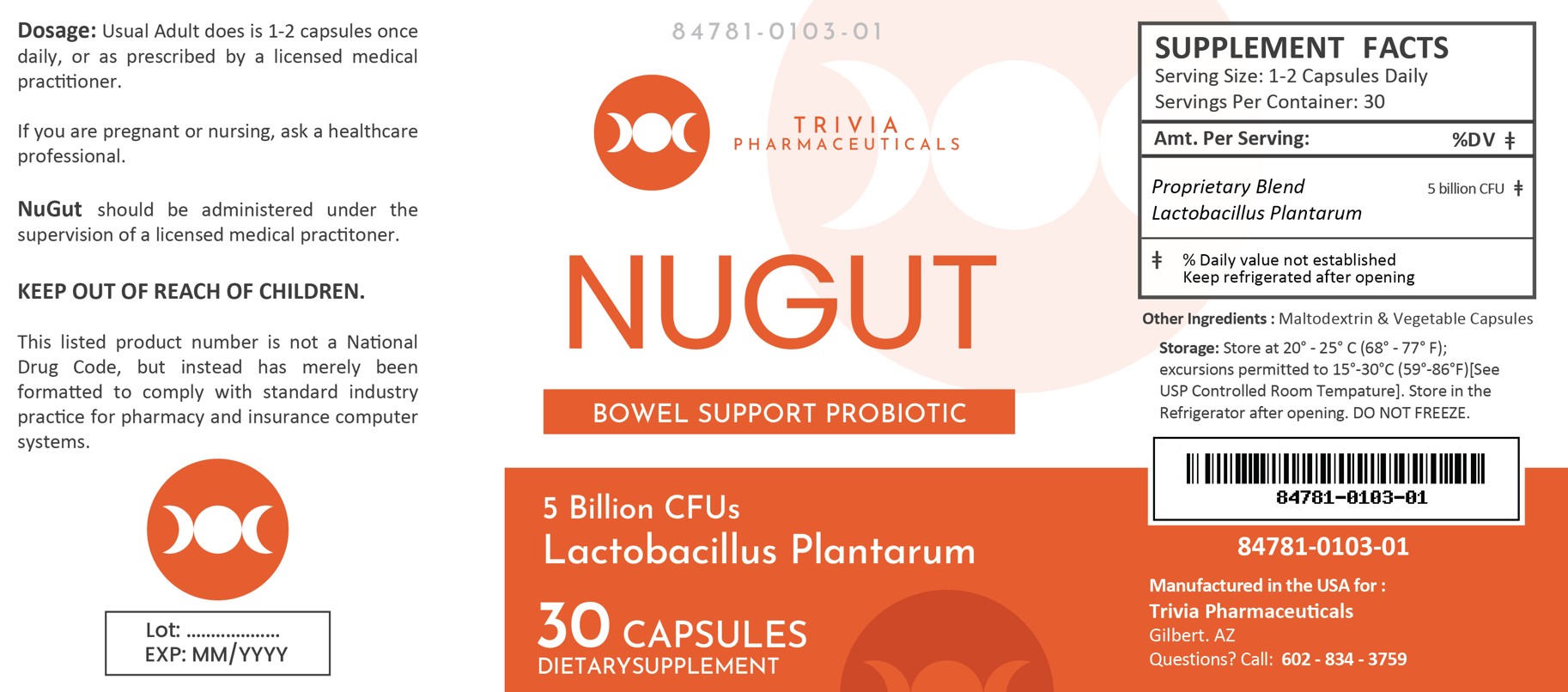 DRUG LABEL: NUGUT
NDC: 84781-103 | Form: CAPSULE
Manufacturer: Trivia Pharmaceuticals, LLC
Category: other | Type: Dietary Supplement
Date: 20250304

ACTIVE INGREDIENTS: LACTOBACILLUS PLANTARUM 299 5000000000 [CFU]/1 1

NuGut Capsules
Bowel Support Probiotic

Health Claim:

NuGut Capsules Dietary Supplement

Description:

NuGut is an orally administered prescription probiotic formulation for the clinical dietary management of suboptimal nutritional status in patients where advanced supplementation is required and nutritional supplementation in physiologically stressful conditions for maintenance of good health is needed.

NuGut should be administered under the supervision of a licensed medical practitioner.

This listed product is not a National Drug Code, but instead has merely been formatted to comply with standard industry practice for pharmacy and insurance computer systems.

Warning and Precautions:

This product is contraindicated in patients with a known hypersensitivity to any of the ingredients.

NuGut should only be used under the direction and supervision of a licensed medical practitioner. Use with caution in patients that may have a medical condition, are pregnant, lactating, trying to conceive, under the age of 18, or taking medications.

Dosage and Administration:

Usual adult dose is 1-2 capsules by mouth daily with or without food.

How Supplied:

NuGut is supplied as clear capsules dispensed in plastic bottles of 30 ct.

84781-103-01

Reserved for Professional Recommendation

All prescriptions using this product shall be pursuant to state statutes as applicable. This is not an Orange Book product. This product may be administered only under a physician’s supervision. There are no implied or explicit claims on therapeutic equivalence.

Manufactured for:
Trivia Pharmaceuticals

Gilbert, AZ

Storage:

Handling (before opening):
Product is sensitive to moisture and heat. Keep bottle tightly closed in a dry, cool place. Store at 20oC to 25oC (68oF to 77oF).

Handling (after opening):
Store in the refrigerator after opening, DO NOT FREEZE. Store at 2oC to 8oC (35oF to 46oF). Call your doctor about side effects. You may report side effects to FDA at 1-800-FDA-1088.